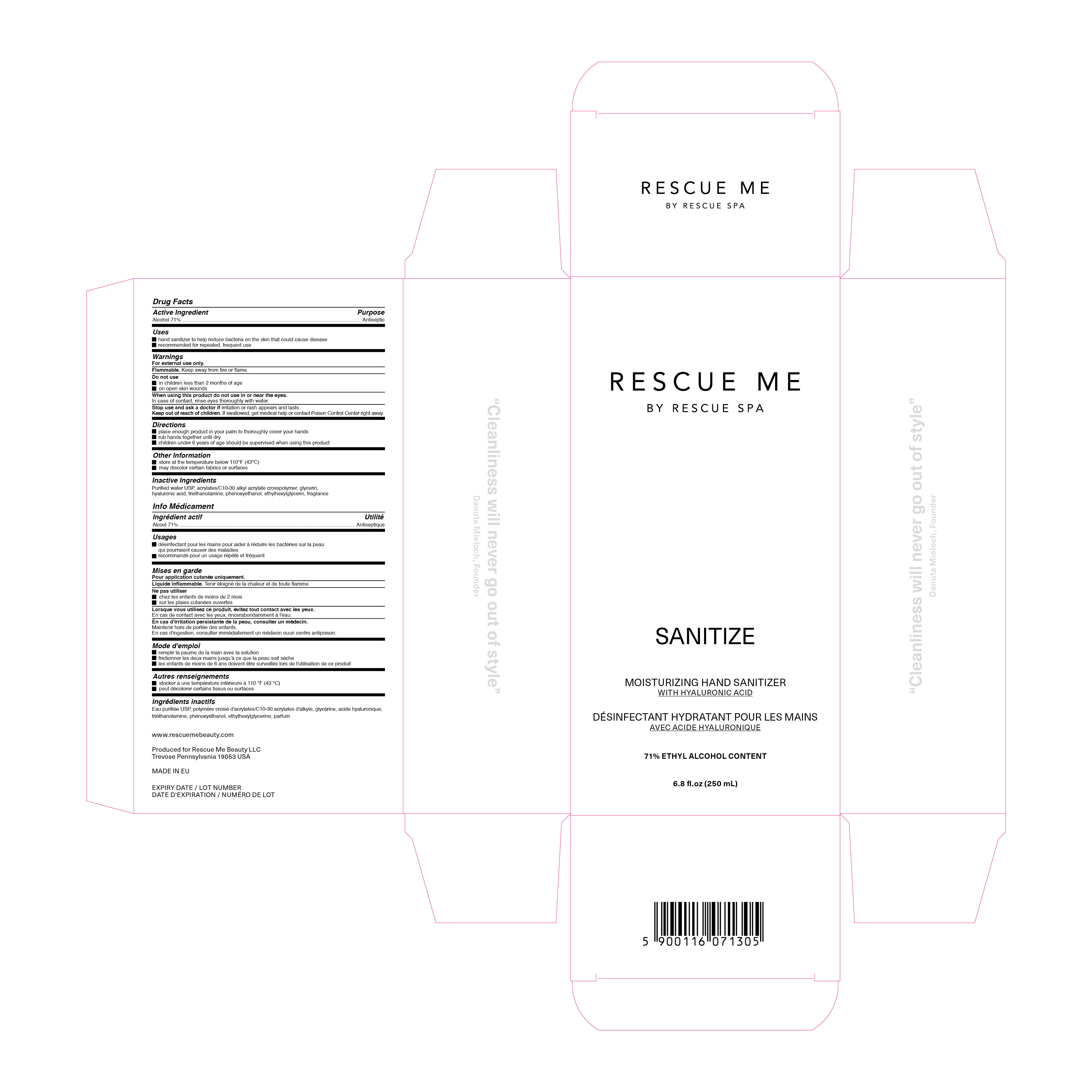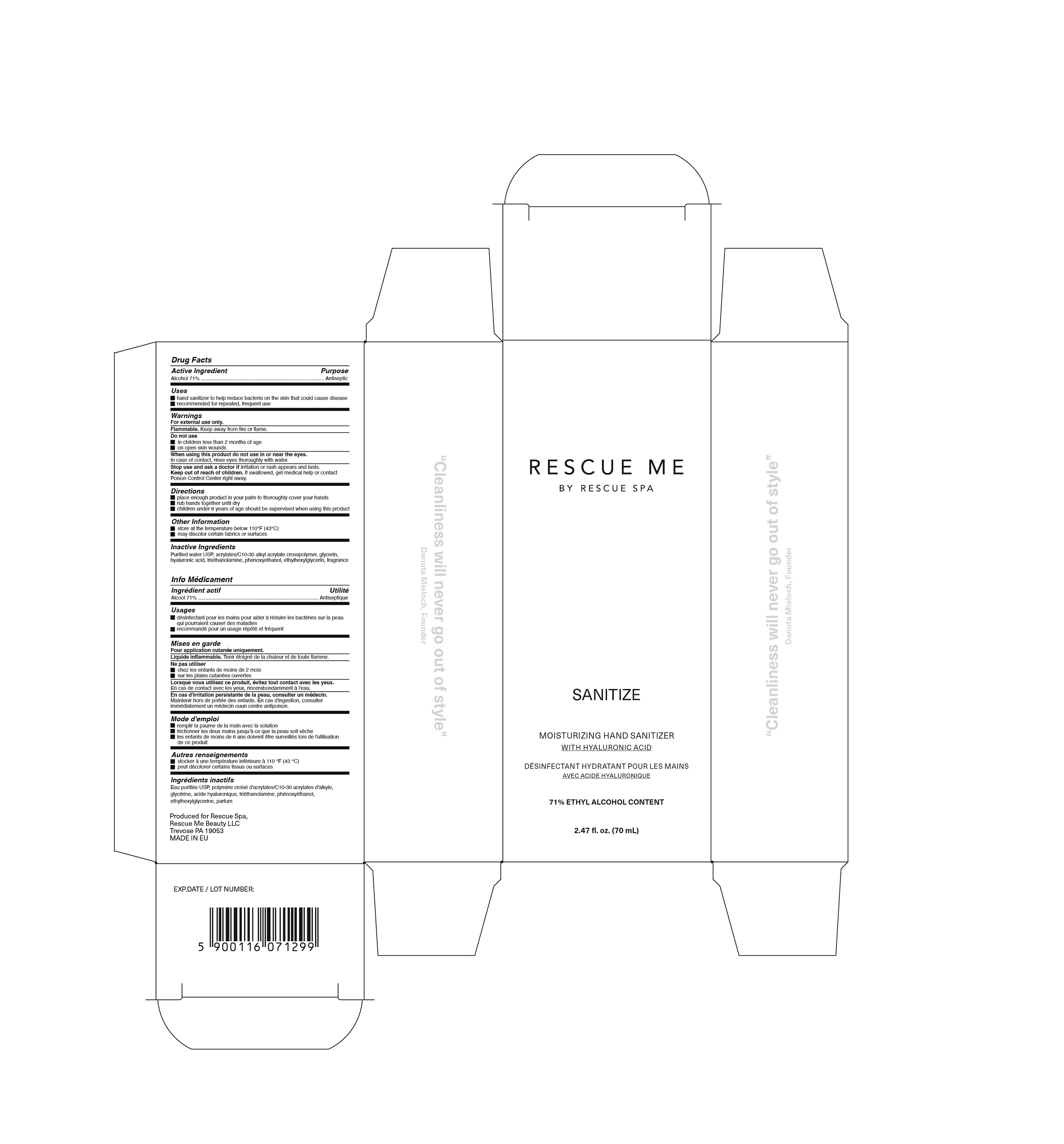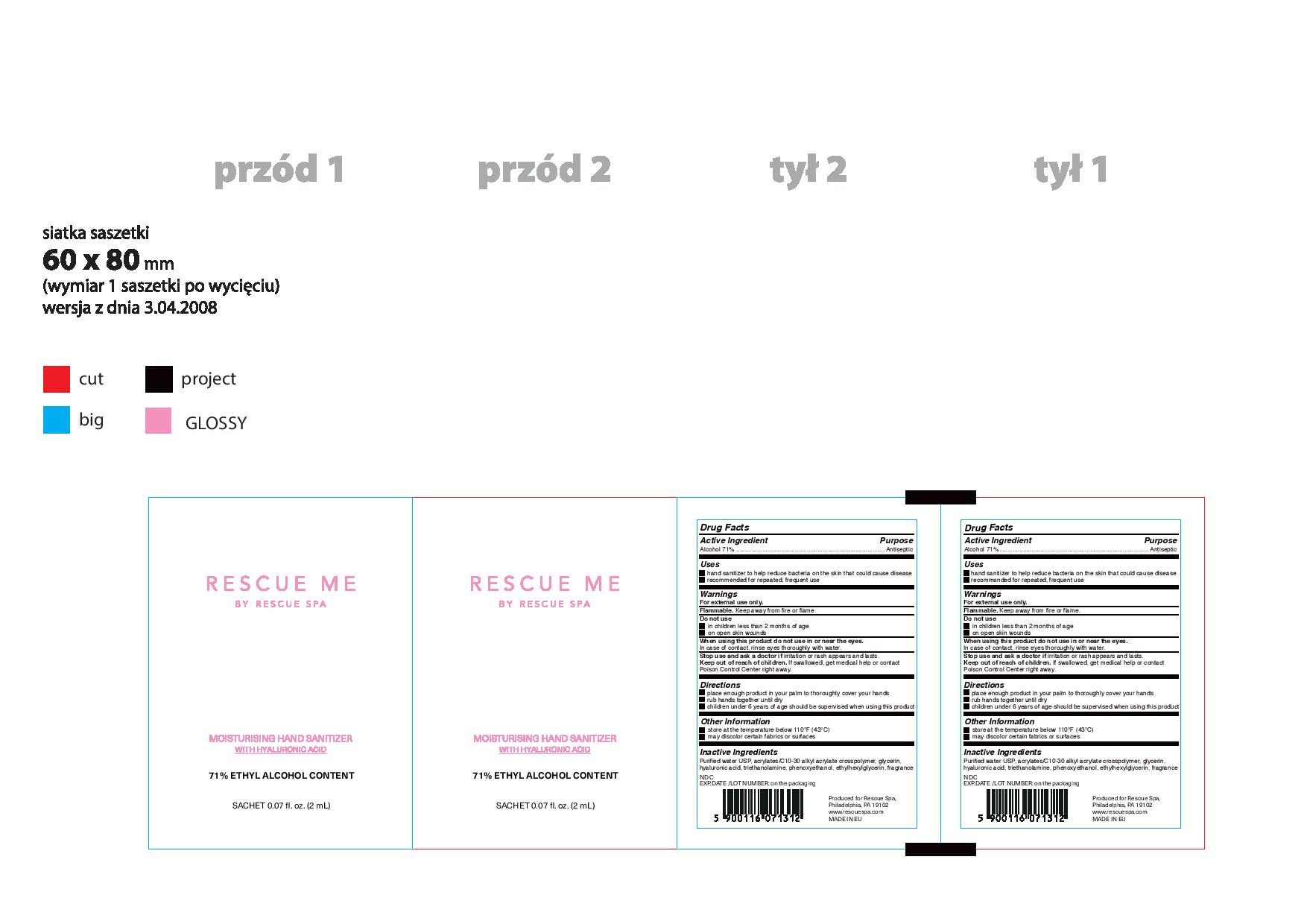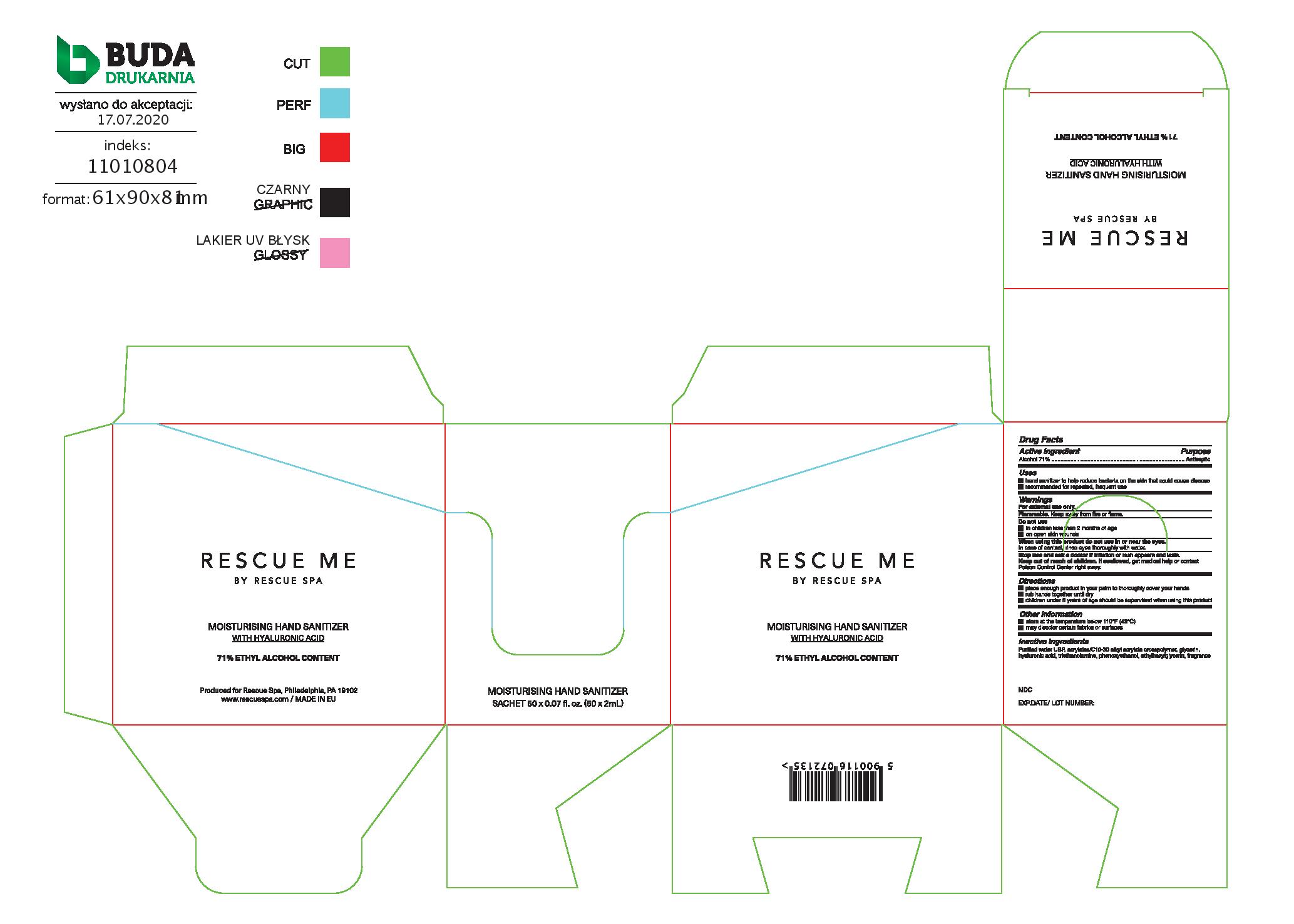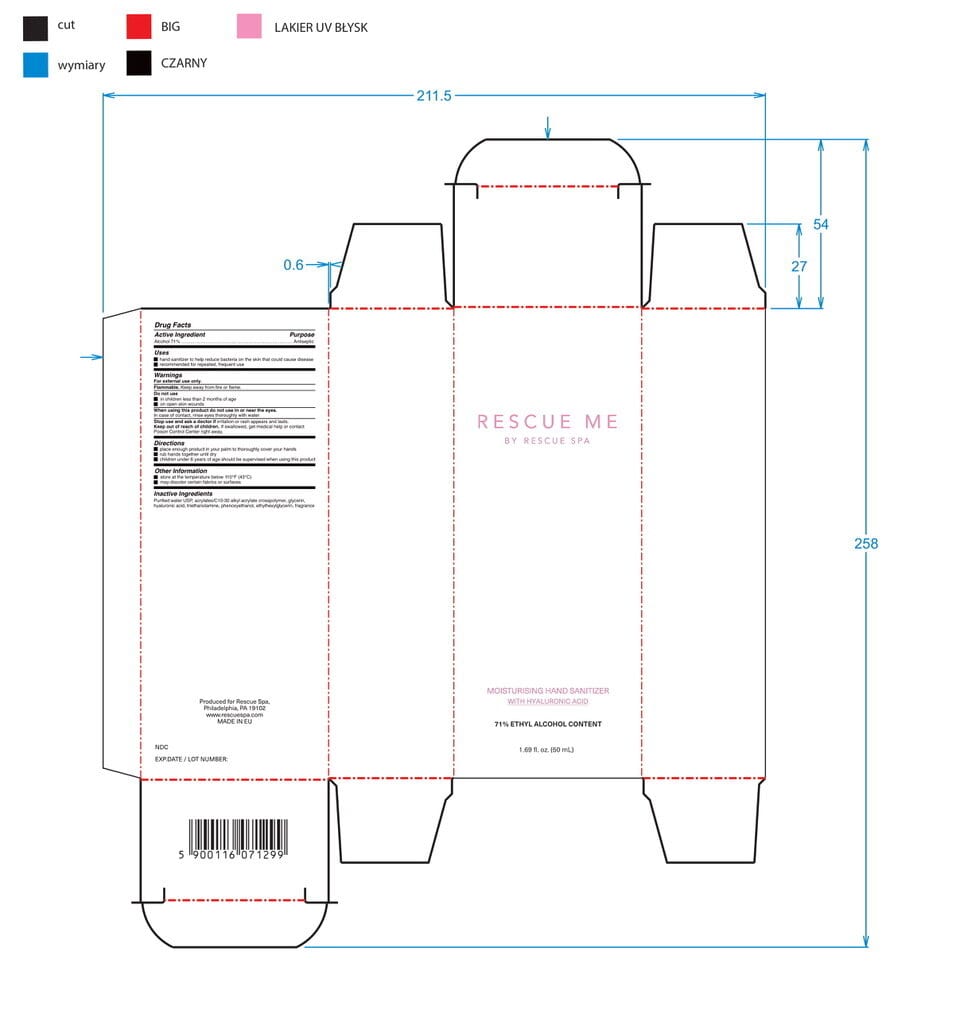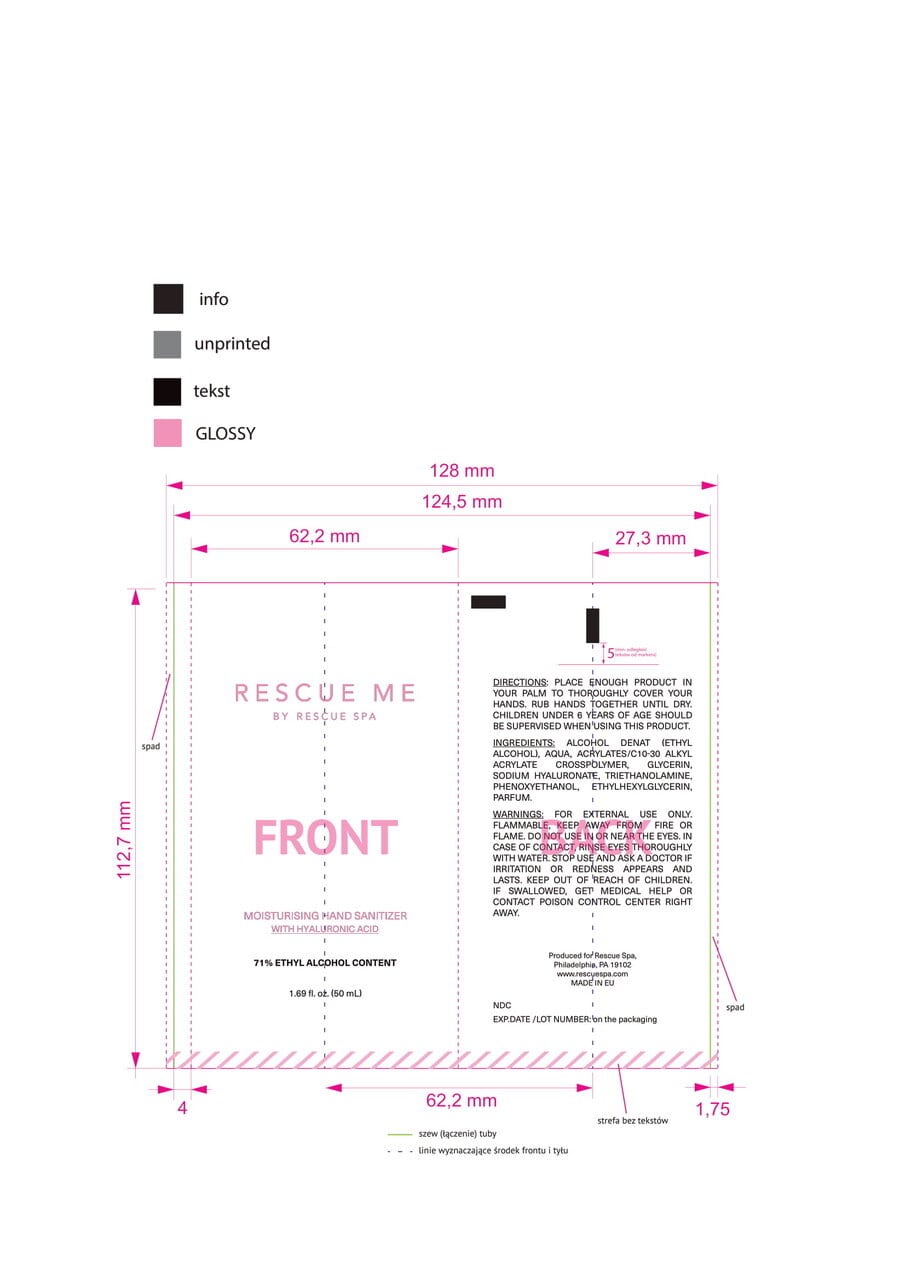 DRUG LABEL: Moisturising Hand Sanitizer
NDC: 79535-7001 | Form: GEL
Manufacturer: RESCUE SPA, INC.
Category: otc | Type: HUMAN OTC DRUG LABEL
Date: 20220329

ACTIVE INGREDIENTS: ALCOHOL 71 mL/100 mL
INACTIVE INGREDIENTS: HYALURONIC ACID 0.001 mL/100 mL; PHENOXYETHANOL 0.0009 mL/100 mL; GLYCERIN 1.2 mL/100 mL; TROLAMINE 0.2 mL/100 mL; WATER; ETHYLHEXYLGLYCERIN 0.0001 mL/100 mL; CARBOMER INTERPOLYMER TYPE A (55000 CPS) 0.8 mL/100 mL

Rescue Me Moisturizing Hand Sanitizer

Active Ingredient(s)

Alcohol 71% v/v. Purpose: Antiseptic

Purpose

Antiseptic, Hand Sanitizer

Use

- Hand Sanitizer to help reduce bacteria that potentially can cause disease.
- Recommended for repeated, frequent use.

Warnings

For external use only. Flammable. Keep away from fire or flame

Do not use

- in children less than 2 months of age
- on open skin wounds

When using this product do not use in or near the eyes. In case of contact, rinse eyes thoroughly with water.
Stop use and ask a doctor if irritation or rash appears and lasts.
Keep out of reach of children. If swallowed, get medical help or contact a Poison Control Center right away.

Stop use and ask a doctor if irritation or rash appears and lasts.

Keep out of reach of children. If swallowed, get medical help or contact a Poison Control Center right away.

Directions

- Place enough product in your palm to thoroughly cover your hands.
- Rub hands together until dry.
- Children under 6 years of age should be supervised when using this product.

Other information

- Store at the temperature below 110F (43C)
- May discolor certain fabrics or surfaces

Inactive ingredients

purified water USP, acrylates/c10-30 alkyl acrylates crosspolymer, glycerin, hyaluronic acid, triethanolamine, phenoxyethanol, ethylhexylglycerin, fragrance

Package Label - Principal Display Panel

Rescue Me by Rescue Spa

Mositurising Hand Sanitizer

bottle 250mL

Rescue Me by Rescue Spa

Mositurising Hand Sanitizer

tube 70mL

Rescue Me by Rescue Spa

Mositurising Hand Sanitizer

Sachet 50 x 0.07 fl. oz. (50 x 2 mL)

Rescue Me by Rescue Spa

Mositurising Hand Sanitizer

1.69 fl.oz. / 50 mL